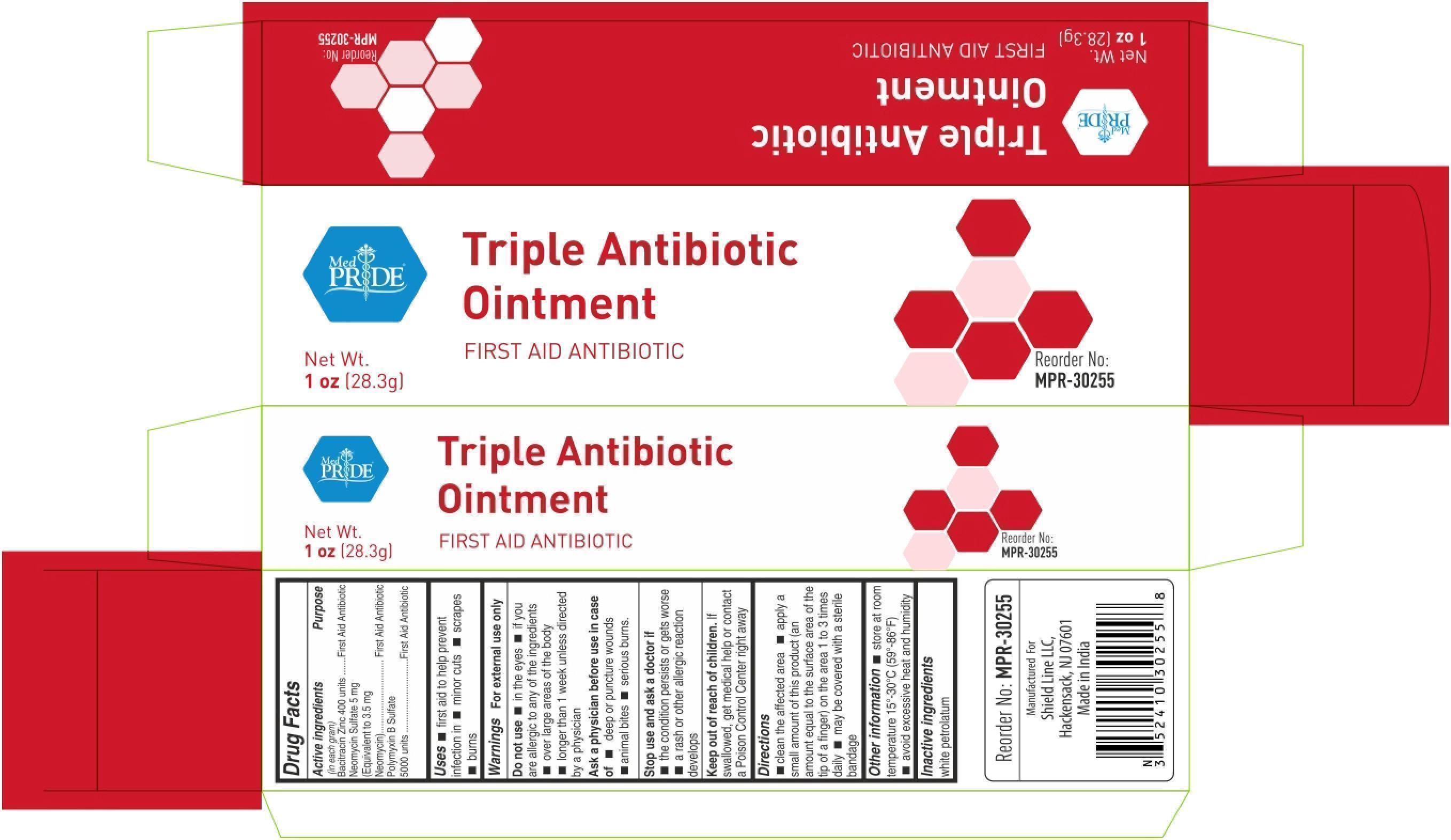 DRUG LABEL: dabur
NDC: 68747-3025 | Form: OINTMENT
Manufacturer: Dabur India Limited
Category: otc | Type: HUMAN OTC DRUG LABEL
Date: 20251118

ACTIVE INGREDIENTS: BACITRACIN ZINC 400 [USP'U]/1 g; NEOMYCIN SULFATE 3.5 mg/1 g; POLYMYXIN B SULFATE 5000 [USP'U]/1 g
INACTIVE INGREDIENTS: PETROLATUM

Triple Antibiotic

Active ingredients (in each gram)

Bacitracin Zinc 400 units

Neomycin Sulfate 5 mg (Equivalent to 3.5 mg Neomycin)

Polymyxin B sulfate 5000 units

Purpose

First Aid AntibioticFirst Aid AntibioticFirst Aid Antibiotic

Uses

■ first aid to help prevent infection in ■ minor cuts ■ scrapes ■ burns

Warnings

For external use only

Do not use

■ in the eyes ■ if you are allergic to any of the ingredients ■ over large areas of the body ■ longer than 1 week unless directed by a doctor

Ask a physician before use in case of

■ deep or puncture wounds ■ animal bites ■ serious burns

Stop use and consult a doctor if

■ the condition persists or gets worse ■ a rash or other allergic reaction develops

Keep out of reach of children. If swallowed, get medical help or contact a Poison Control Center right away.

Directions

■ clean the affected area ■ apply a small amount of this product (an amount equal to the surface area of the tip of a finger) on the area 1 to 3 times daily ■ may be covered with a sterile bandage

Other Information

■ store at room temperature 15-30C (59-86F) ■ avoid excessive heat and humidity

Inactive ingredients

white petrolatum